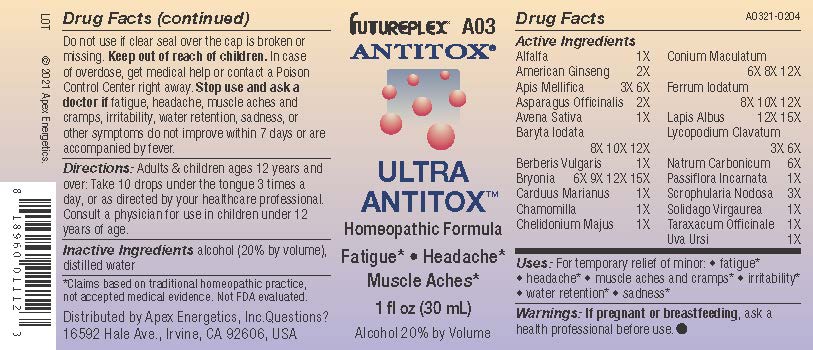 DRUG LABEL: A03
NDC: 63479-0103 | Form: SOLUTION/ DROPS
Manufacturer: Apex Energetics Inc.
Category: homeopathic | Type: HUMAN OTC DRUG LABEL
Date: 20240108

ACTIVE INGREDIENTS: BRYONIA ALBA ROOT 15 [hp_X]/1 mL; APIS MELLIFERA 6 [hp_X]/1 mL; ASPARAGUS 2 [hp_X]/1 mL; AVENA SATIVA FLOWERING TOP 1 [hp_X]/1 mL; ALFALFA 1 [hp_X]/1 mL; AMERICAN GINSENG 2 [hp_X]/1 mL; FERROUS IODIDE 12 [hp_X]/1 mL; SODIUM CARBONATE 6 [hp_X]/1 mL; BARIUM IODIDE 12 [hp_X]/1 mL; PASSIFLORA INCARNATA FLOWERING TOP 1 [hp_X]/1 mL; CONIUM MACULATUM FLOWERING TOP 12 [hp_X]/1 mL; LYCOPODIUM CLAVATUM SPORE 6 [hp_X]/1 mL; SCROPHULARIA NODOSA 3 [hp_X]/1 mL; TARAXACUM OFFICINALE 1 [hp_X]/1 mL; CALCIUM HEXAFLUOROSILICATE 15 [hp_X]/1 mL; ARCTOSTAPHYLOS UVA-URSI LEAF 1 [hp_X]/1 mL; MATRICARIA CHAMOMILLA 1 [hp_X]/1 mL; SOLIDAGO VIRGAUREA FLOWERING TOP 1 [hp_X]/1 mL; BERBERIS VULGARIS ROOT BARK 1 [hp_X]/1 mL; MILK THISTLE 1 [hp_X]/1 mL; CHELIDONIUM MAJUS 1 [hp_X]/1 mL
INACTIVE INGREDIENTS: ALCOHOL; WATER

A03

Active Ingredients
Alfalfa | 1X
American Ginseng | 2X
Apis Mellifica | 3X 6X
Asparagus Officinalis | 2X
Avena Sativa | 1X
Baryta Iodata | 8X 10X 12X
Berberis Vulgaris | 1X
Bryonia | 6X 9X 12X 15X
Carduus Marianus | 1X
Chamomilla | 1X
Chelidonium Majus | 1X
Conium Maculatum | 6X 8X 12X
Ferrum Iodatum | 8X 10X 12X
Lapis Albus | 12X 15X
Lycopodium Clavatum | 3X 6X
Natrum Carbonicum | 6X
Passiflora Incarnata | 1X
Scrophularia Nodosa | 3X
Solidago Virgaurea | 1X
Taraxacum Officinale | 1X
Uva Ursi | 1X

INDICATIONS AND USAGE

Uses:

For temporary relief of minor:

fatigue*

headache*

muscle aches and cramps*

irritability*

water retention*

sadness*

*Claims based on traditional homeopathic practice, not accepted medical evidence. Not FDA evaluated.

Warnings:

PREGNANCY OR BREAST FEEDING

If pregnant or breastfeeding, ask a health professional before use.

Do not use if clear seal over the cap is broken or missing.

Keep out of reach of children. In case of overdose, get medical help or contact a Poison Control Center right away.

Stop use and ask a doctor if fatigue, headache, muscle aches and cramps, irritability, water retention, sadness, or other symptoms do not improve within 7 days or are accompanied by fever.

Directions:

Adults & children ages 12 years and over: Take 10 drops under the tongue 3 times a day, or as directed by your healthcare professional. Consult a physician for use in children under 12 years of age

.

Inactive Ingredients

alcohol (20% by volume), distilled water

Distributed by Apex Energetics, Inc. Questions?

16592 Hale Ave., Irvine, CA 92606, USA

PACKAGE LABEL

FUTUREPLEX® A03

ANTITOX®

ULTRA ANTITOX™

Homeopathic Formula

Fatigue*

Headache*

Muscle Aches*

1 fl oz (30 mL)

Alcohol 20% by Volume